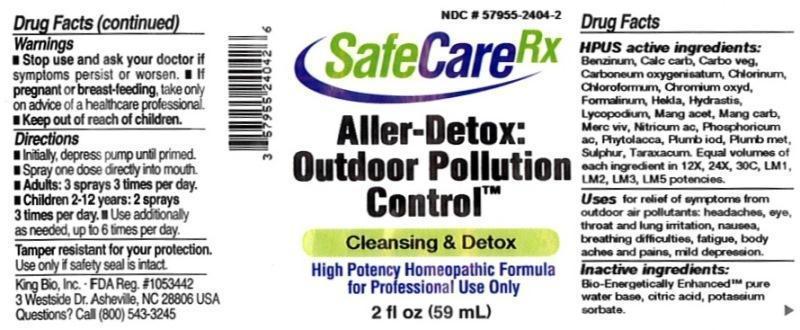 DRUG LABEL: Aller Detox Outdoor Pollution Control
NDC: 57955-2404 | Form: LIQUID
Manufacturer: King Bio Inc.
Category: homeopathic | Type: HUMAN OTC DRUG LABEL
Date: 20150616

ACTIVE INGREDIENTS: BENZENE 12 [hp_X]/59 mL; OYSTER SHELL CALCIUM CARBONATE, CRUDE 12 [hp_X]/59 mL; ACTIVATED CHARCOAL 12 [hp_X]/59 mL; CARBON MONOXIDE 12 [hp_X]/59 mL; CHLORINE 12 [hp_X]/59 mL; CHLOROFORM 12 [hp_X]/59 mL; CHROMIC OXIDE 12 [hp_X]/59 mL; FORMALDEHYDE 12 [hp_X]/59 mL; HEKLA LAVA 12 [hp_X]/59 mL; GOLDENSEAL 12 [hp_X]/59 mL; LYCOPODIUM CLAVATUM SPORE 12 [hp_X]/59 mL; MANGANESE ACETATE TETRAHYDRATE 12 [hp_X]/59 mL; MANGANESE CARBONATE 12 [hp_X]/59 mL; MERCURY 12 [hp_X]/59 mL; NITRIC ACID 12 [hp_X]/59 mL; PHOSPHORIC ACID 12 [hp_X]/59 mL; PHYTOLACCA AMERICANA ROOT 12 [hp_X]/59 mL; LEAD IODIDE 12 [hp_X]/59 mL; LEAD 12 [hp_X]/59 mL; SULFUR 12 [hp_X]/59 mL; TARAXACUM OFFICINALE 12 [hp_X]/59 mL
INACTIVE INGREDIENTS: WATER; ANHYDROUS CITRIC ACID; POTASSIUM SORBATE

Aller Detox Outdoor Pollution Control™

ACTIVE INGREDIENT

Drug Facts__________________________________________________________________________________________________________

HPUS active ingredients: Benzinum, Calcarea carbonica, Carbo vegetabilis, Carboneum oxygenisatum, Chlorinum, Chloroformum, Chromium oxydatum, Formalinum, Hekla lava, Hydrastis canadensis, Lycopodium clavatum, Manganum aceticum, Manganum carbonicum, Mercurius vivus, Nitricum acidum, Phosphoricum acidum, Phytolacca decandra, Plumbum iodatum, Plumbum metallicum, Sulphur, Taraxacum. Equal volumes of each ingredient in 12X, 24X, 30C, LM1, LM2, LM3, LM5 potencies.

INDICATIONS AND USAGE

Uses for relief of symptoms from outdoor air pollutants: headaches, eye, throat and lung irritation, nausea, breathing difficulties, fatigue, body aches and pains, mild depression.

Inactive Ingredients:

Bio-Energetically Enhanced™ pure water, citric acid and potassium sorbate.

Warnings

- Stop use and ask your doctor if symptoms persist or worsen.
- If pregnant or breast-feeding, take only on advice of a healthcare professional.

- Keep out of reach of children.

Directions

- Initially, depress pump until primed.
- Spray one dose directly into mouth.
- Adults: 3 sprays 3 times per day
- Children 2-12 years: 2 sprays 3 times per day.
- Use additionally as needed, up to 6 times per day.

OTHER SAFETY INFORMATION

Tamper resistant for your protection. Use only if safety seal is intact.

PURPOSE

Uses for relief of symptoms from outdoor air pollutants:

- headaches
- eye
- throat and lung irritation
- nausea
- breathing difficulties
- fatigue
- body aches and pains
- mild depression